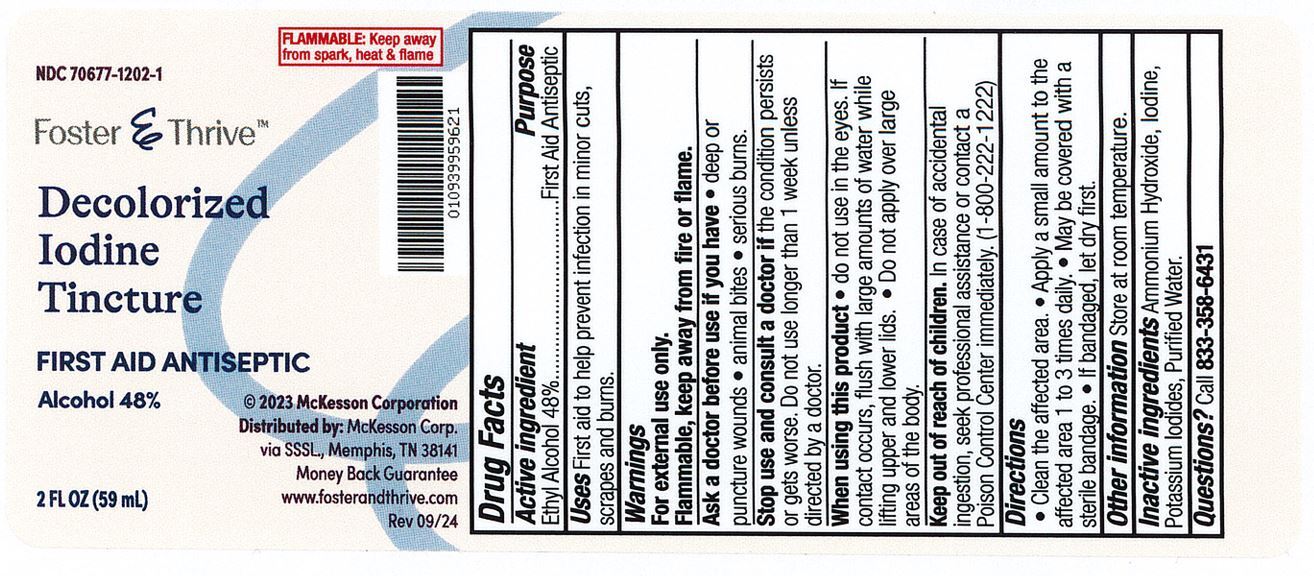 DRUG LABEL: Foster and Thrive Decolorized Iodine
NDC: 70677-1202 | Form: LIQUID
Manufacturer: Strategic Sourcing Services, LLC
Category: otc | Type: HUMAN OTC DRUG LABEL
Date: 20241217

ACTIVE INGREDIENTS: ALCOHOL 0.48 mL/1 mL
INACTIVE INGREDIENTS: POTASSIUM IODIDE; AMMONIA; WATER; IODINE

Foster & Thrive Decolorized Iodine

ACTIVE INGREDIENT

Ethyl Alcohol 48%

PURPOSE

First Aid Antiseptic

INDICATIONS AND USAGE

First aid to help prevent skin infection in minor cuts, scrapes and burns.

WARNINGS

For External Use Only.

When using this product:

Flammable, keep away from fire or flame

When using this product

Do not use in the eyes. If contact occurs, flush with large amounts of water while lifting upper and lower lids. Do not or apply over large areas of the body.

Keep out of reach of children. In case of accidential ingestion, seek professional assistance or contact a Poison Control Center immediately. (1-800-222-1222)

DOSAGE AND ADMINISTRATION

Clean the affected area, apply a small amount on the area 1 to 3 times daily. May be covered with a sterile bandage. If bandaged, let dry first.

INACTIVE INGREDIENT

- Ammonium Hydroxide
- Iodine
- Potassium Iodide
- Purified Water

Questions?

Call 833-358-6431